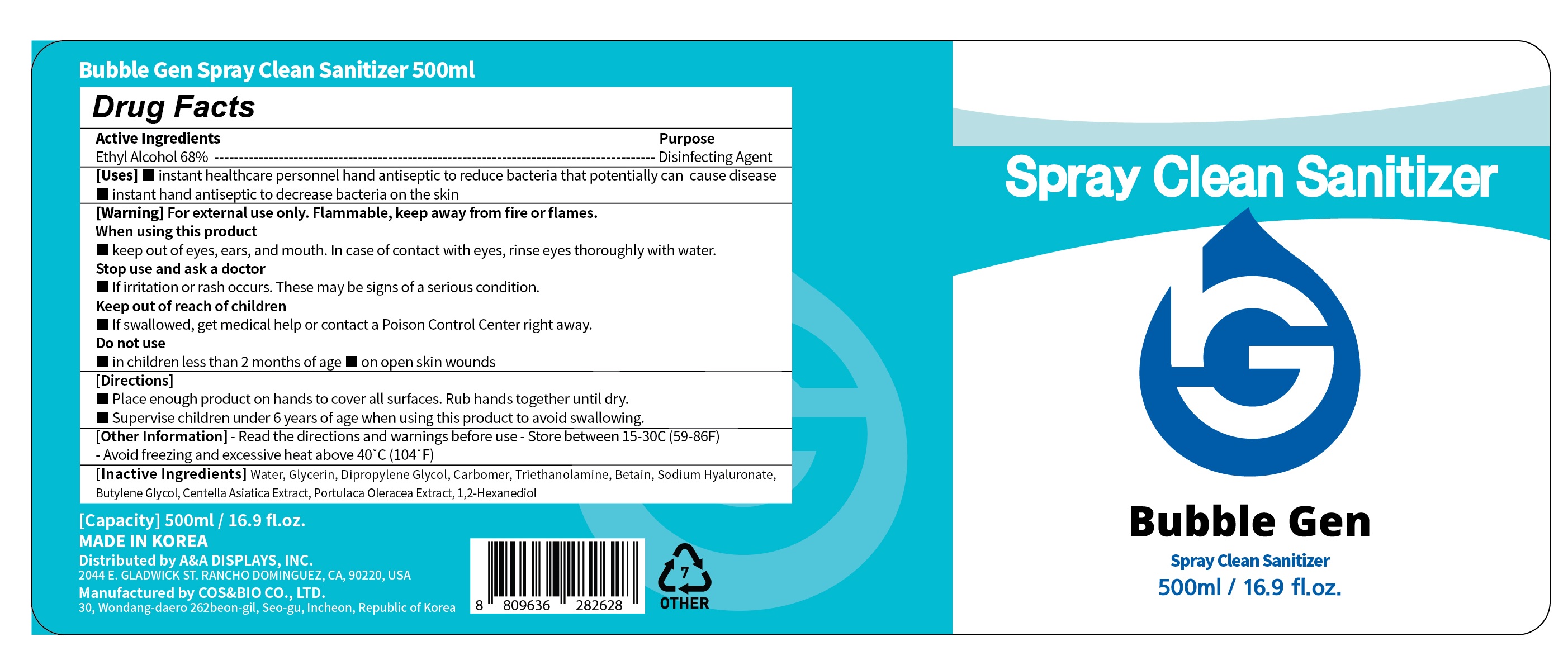 DRUG LABEL: Bubble Gen SprayClean Sanitizer 500ml
NDC: 76770-5068 | Form: GEL
Manufacturer: COS&BIO Co Ltd
Category: otc | Type: HUMAN OTC DRUG LABEL
Date: 20200708

ACTIVE INGREDIENTS: ALCOHOL 340 mL/500 mL
INACTIVE INGREDIENTS: CENTELLA ASIATICA; PORTULACA OLERACEA WHOLE; HYALURONATE SODIUM; GLYCERIN; CARBOMER HOMOPOLYMER, UNSPECIFIED TYPE; WATER; TROLAMINE; DIPROPYLENE GLYCOL; BETAINE; BUTYLENE GLYCOL; 1,2-HEXANEDIOL

[COS&BIO Co Ltd] Bubble Gen Spray Clean Sanitizer 500ml | Bottle+Pump | 76770-5068-1